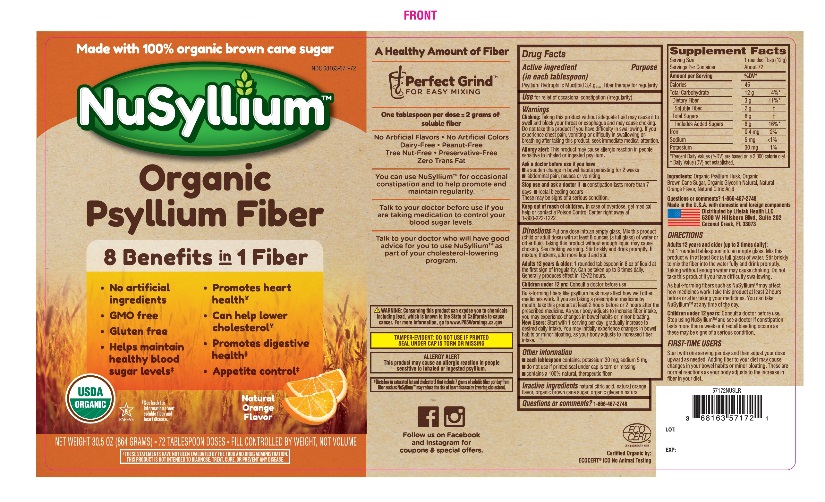 DRUG LABEL: Natural Orange Flavor
NDC: 68163-571 | Form: POWDER
Manufacturer: Raritan Pharmaceuticals Inc
Category: otc | Type: HUMAN OTC DRUG LABEL
Date: 20250408

ACTIVE INGREDIENTS: PSYLLIUM HUSK 3.4 g/12 g
INACTIVE INGREDIENTS: ANHYDROUS CITRIC ACID; RAW SUGAR; GLYCERIN

Active ingredient (in each TABLESPOON)

Psyllium Hydrophilic Mucilloid 3.4g

Purpose

Fiber therapy for regularity

Use

for relief of occasional constipation (regularity)

Warnings

Choking: Taking this product without adequate fluid may cause it to swell and block your throat or esophagus and may cause choking. Do not take this product if you have difficulty in swallowing. If you experience chest pain, vomiting or difficulty in swallowing or breathing after taking this product, seek immediate medical attention.

Allergy alert:

This product may cause allergic reaction in people sensitive to inhaled or ingested psyllium.

Ask a doctor before use if you have

- a sudden change in bowel habits persisting for 2 weeks.
- abdominal pain, nausea or vomiting

Stop use and ask a doctor

- constipation lasts more than 7 days
- rectal bleeding occurs

These may be sings of a serious condition

Keep Out of Reach of Children

In case of overdose, get medical help or contact a Poison Control Center right away at 1-800-222-1222.

Directions:

Put one dose into an empty glass. Mix this product (child or adult dose) with at least 8 ounces (a full glass) of water or other fluid.

Taking this product without enough liquid may cause choking. See choking warning. Stir briskly and drink promptly. If mixture thickness, add more liquid and stir.

Adults 12 years & older: 1 rounded TABLESPOON in 8 oz of liquid at the first sign of irregularity. Can be taken up to 3 times daily. Generally produces effect in 12-72 hours.

Children under 12 yrs: Consult a doctor before use

Bulk-forming fibers like psyllium husk may affect how well other medicines work. If you are taking a prescription medicine by mouth, take this product at least 2 hours before or 2 hours after the prescribed medicine. As your body adjusts to increase fiber intake, you may experience changes in bowel habits or minor bloating.

New Users: Start with 1 serving per day, gradually increase to desired daily intake. You may initially experience changes in bowel habits or minor bloating as your body adjusts to increased fiber intake.

Other information

- each tablespoon contains: potassium 35 mg; sodium 5 mg
- Store at room temperature tightly closed to protect from humidity
- Do not use if printed seal under cap is torn or missing
- Contains a 100% natural, therapeutic fiber

‡ Diets low in saturated fat and cholesterol that include 7 grams of soluble fiber per day from fiber such as NuSyllium may reduce the risk of heart disease by lowering cholesterol.

*These statements have not been evaluated by the Food and Drug Administration. This product is not intended to diagnose, treat, cure or prevent any disease.

TAMPER-EVIDENT: DO NOT USE IF PRINTED SEAL UNDER CAP IS TORN OR MISSING

Questions or comments?

1-866-467-2748

Inactive ingredients

Natural citric acid, natural flavors, Organic Brown Cane Sugar, Organic Vegetable Glycerin.

Principal Display Panel

NDC 68163-571-72

NuSyllium

Natural Orange Flavor

Organic Natural Fiber

100% Organic Certified Psyllium

Perfect Grind For Easy Mixing™

USDA ORGANIC

NO ARTIFICIAL INGREDIENTS

100% Natural Fiber Supplement

Fiber Laxative for Regularity

Made with 100% Organic Brown Cane Sugar

Folks are taking about the Benefits of NuSyllium Organic Natural Fiber!

- You can use NuSyllium to feel less hungry between meals.
- Maintain healthy blood sugar levels by using NuSyllium Ultra as part of your sugar free diet*. Talk to your doctor before use if you are taking medication to control your blood sugar levels.
- Organic NuSyllium is a great choice for promoting and maintain digestive health. You can use NuSyllium Ultra for occasional constipation and to help promote and maintain regularity.
- Did you know that one dose of NuSyllium Ultra contains 2 gm. of soluble fiber? You can use it for lowering cholesterol and promoting heart health*.

No Artificial Flavors, Peanut-free

No Artificial Colors, Tree Nut-free

GMO-free, Preservative-free

Gluten-free, Zero Trans Fat

Diary-free

NET WT 30.5 OZ (864 g) 72 DOSES

Fill controlled by weight, not volume

Made in the U.S.A. with domestic and foreign components.

Distributed by: Lifelab Health LLC

6574 N.State Road #7 361

Coconut Creek, FL 33073